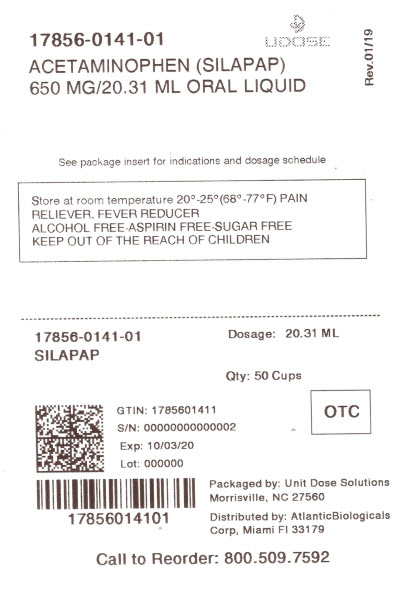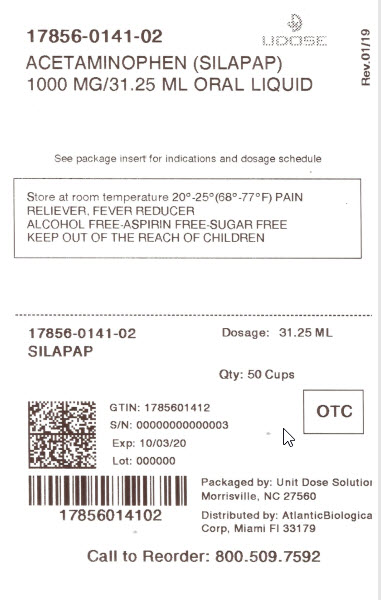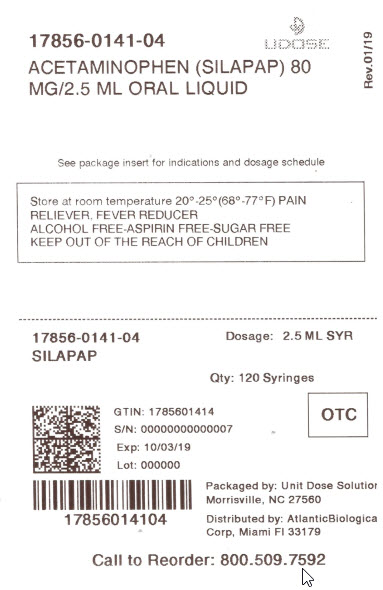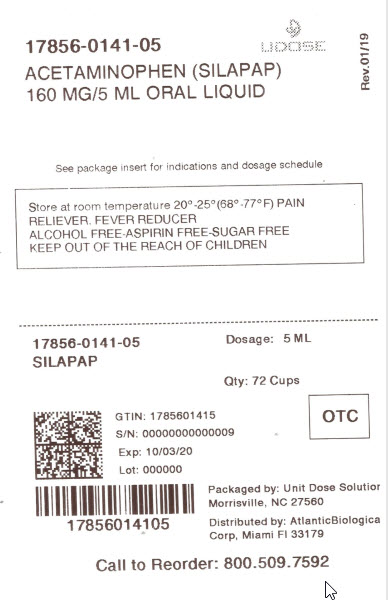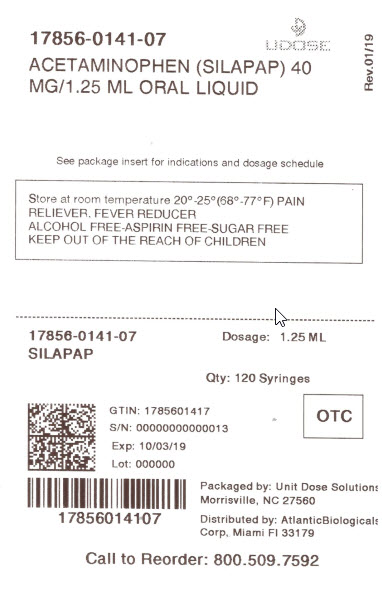 DRUG LABEL: Childrens Silapap
NDC: 17856-0141 | Form: LIQUID
Manufacturer: ATLANTIC BIOLOGICALS CORP.
Category: otc | Type: HUMAN OTC DRUG LABEL
Date: 20210115

ACTIVE INGREDIENTS: ACETAMINOPHEN 160 mg/5 mL
INACTIVE INGREDIENTS: ANHYDROUS CITRIC ACID; D&C RED NO. 33; FD&C RED NO. 40; METHYLPARABEN; PROPYLENE GLYCOL; SACCHARIN SODIUM; SODIUM BENZOATE; WATER

Children's Silapap Liquid

Active Ingredient: Acetaminophen 160 mg (in each 5 mL (TSP))

Purpose: Pain reliever/fever reducer

INDICATIONS AND USAGE

Uses To reduce fever and for the temporary relief of minor aches and pains due to:

- Headache
- Muscular aches
- Backache
- Minor pain of arthritis
- The common cold
- Toothache
- Premenstrual and menstrual cramps

Warnings

Liver Warning:This product contains acetaminophen. Severe liver damage may occur if you take:

- more than 5 doses in 24 hours, which is the maximum daily amount
- with other drugs containing acetaminophen
- 3 or more alcoholic drinks every day while using this product

Sore throat warning: if sore throat is severe, persists for more than 2 days, is accompanied or followed by fever, headache, rash, nausea or vomiting, consult a doctor promptly.

Alcohol warning:If the user consumes 3 or more alcoholic drinks every day, ask your doctor whether you should take acetaminophen or other pain relievers/fever reducers.

Do not use

- with any other product drug containing acetaminophen (prescription or nonprescription). If you are not sure whether a drug contains acetaminophen, ask a doctor or pharmacist.
- if the user is allergic to acetaminophen or any of the inactive ingredients in this product

When using this product

- do not exceed recommended dose (see overdose warning)

Stop use and ask a doctor if

- new symptoms occur
- redness or swelling is present
- pain gets worse or lasts for more than 5 days
- fever gets worse or lasts for more than 3 days
- These could be signs of a serious condition

If pregnant or breast-feeding, ask a health professional before use.

Keep out of reach of children.

OVERDOSAGE

Overdose Warning: In case of overdose, get medical help or contact a Poison Control Center (1800-222-1222) right away. Quick medical attention is critical even if you do not notice any signs of symptoms.

Directions

- do not take more than directed (see overdose warning).
- if needed, repeat dose every 4 hours or as directed by a doctor
- do not give more than 5 doses in 24 hours

children under 2 yrs (under 24 lbs) | ask a doctor
children 2-3 years (24-35 lbs) | 1 teaspoonful (TSP)(5 mL)
children 4-5 years (36-47 lbs) | 1 1/2 teaspoonfuls (TSP)(7.5 mL)
children 6-8 years (48-59 lbs) | 2 teaspoonfuls (TSP)(10 mL)
children 9-10 years (60-71 lbs) | 2 1/2 teaspoonfuls (TSP)(12.5 mL)
children 11 years (72-95 lbs) | 3 teaspoonfuls (TSP)(15 mL)
adults & children 12 years & older | 4 teaspoonfuls (TSP)(20 mL)

Other information
Store at room temperature 20°-25°C (68°-77°F)

Inactive ingredients

citric acid, D&C red no. 33, FD&C red no. 40, cherry flavor, methylparaben, propylene glycol, saccharin sodium, sodium benzoate, and purified water.

Questions

DISTRIBUTED BY:

ATLANTIC BIOLOGICALS CORP.

20101 NE 16TH PLACE

MIAMI, FL 33179